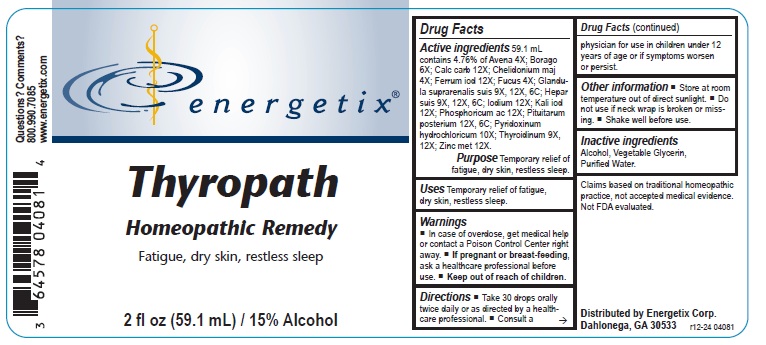 DRUG LABEL: Thyropath
NDC: 64578-0133 | Form: LIQUID
Manufacturer: Energetix Corporation
Category: homeopathic | Type: HUMAN OTC DRUG LABEL
Date: 20250711

ACTIVE INGREDIENTS: AVENA SATIVA FLOWERING TOP 4 [hp_X]/1 mL; BORAGE 6 [hp_X]/1 mL; OYSTER SHELL CALCIUM CARBONATE, CRUDE 12 [hp_X]/1 mL; CHELIDONIUM MAJUS 4 [hp_X]/1 mL; FERROUS IODIDE 12 [hp_X]/1 mL; FUCUS VESICULOSUS 4 [hp_X]/1 mL; SUS SCROFA ADRENAL GLAND 9 [hp_X]/1 mL; PORK LIVER 9 [hp_X]/1 mL; IODINE 12 [hp_X]/1 mL; POTASSIUM IODIDE 12 [hp_X]/1 mL; PHOSPHORIC ACID 12 [hp_X]/1 mL; BOS TAURUS PITUITARY GLAND, POSTERIOR 12 [hp_X]/1 mL; PYRIDOXINE HYDROCHLORIDE 10 [hp_X]/1 mL; THYROID, BOVINE 9 [hp_X]/1 mL; ZINC 12 [hp_X]/1 mL
INACTIVE INGREDIENTS: WATER; ALCOHOL; GLYCERIN

Thyropath

Active ingredients

59.1 mL contains 4.76% of Avena 4X; Borago 6X; Calcarea carb 12X; Chelidonium maj 4X; Ferrum iod 12X; Fucus 4X; Glandula suprarenalis suis 9X, 12X, 6C; Hepar suis 9X, 12X, 6C; Iodium 12X; Kali iod 12X; Phosphoricum acidum 12X; Pituitarum posterium 12X, 6C; Pyridoxinum hydrochloricum 10X; Thyroidinum (Bovine) 9X, 12X; Zincum met 12X.

Claims based on traditional homeopathic practice, not accepted medical evidence. Not FDA evaluated.

INDICATIONS AND USAGE

Uses Temporary relief of fatigue, dry skin, restless sleep.

Warnings

- In case of overdose, get medical help or contact a Poison Control Center right away.
- If pregnant or breast-feeding, ask a healthcare professional before use.

- Keep out of reach of children.

Directions

- Take 30 drops orally twice daily or as directed by a healthcare professional.
- Consult a physician for use in children under 12 years of age or if symptoms worsen or persist.

Other information

- Store at room temperature out of direct sunlight.
- Do not use if neck wrap is broken or missing.
- Shake well before use.

Inactive ingredients Alcohol, Vegetable Glycerin, Purified Water

QUESTIONS

Distributed by
Energetix Corp.
Dahlonega, GA 30533

Questions? Comments?

800.990.7085
www.energetix.com

PACKAGE LABEL

energetix
Thyropath
Homeopathic Remedy
Fatigue, dry skin, restless sleep.
2 fl oz (59.1 mL) 15% Alcohol

PURPOSE

Purpose Temporary relief of fatigue, dry skin, restless sleep.